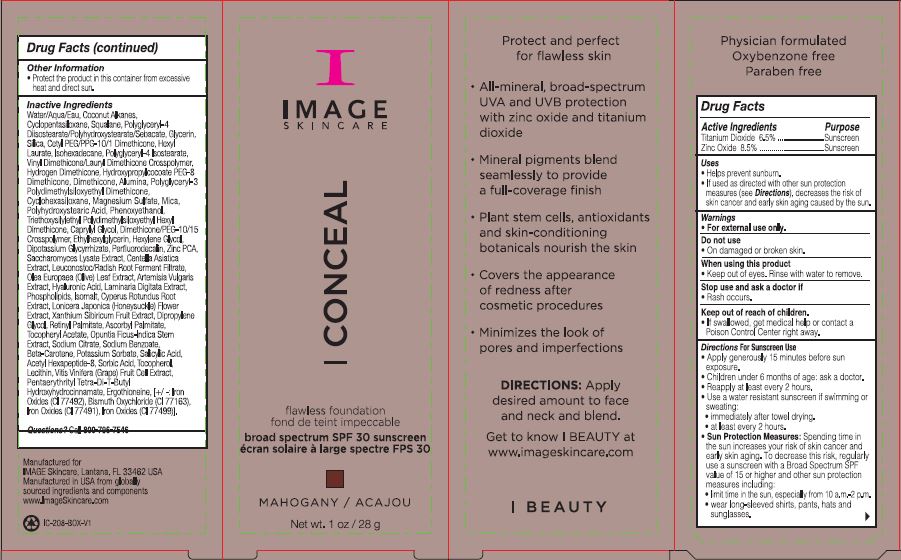 DRUG LABEL: I Conceal Flawless Foundation Broad Spectrum SPF 30 Sunscreen Mahogany
NDC: 62742-4214 | Form: CREAM
Manufacturer: Allure Labs
Category: otc | Type: HUMAN OTC DRUG LABEL
Date: 20241209

ACTIVE INGREDIENTS: ZINC OXIDE 85 mg/1 g; TITANIUM DIOXIDE 65 mg/1 g
INACTIVE INGREDIENTS: POLYGLYCERYL-4 DIISOSTEARATE/POLYHYDROXYSTEARATE/SEBACATE; GLYCERIN; ARTEMISIA VULGARIS WHOLE; GLYCYRRHIZINATE DIPOTASSIUM; PERFLUNAFENE; ZINC PIDOLATE; CENTELLA ASIATICA TRITERPENOIDS; LEUCONOSTOC/RADISH ROOT FERMENT FILTRATE; PENTAERYTHRITOL TETRAKIS(3-(3,5-DI-TERT-BUTYL-4-HYDROXYPHENYL)PROPIONATE); FERROSOFERRIC OXIDE; DIMETHICONE/PEG-10/15 CROSSPOLYMER; CETYL PEG/PPG-10/1 DIMETHICONE (HLB 4); HYDROXYPROPYLCOCOATE PEG-8 DIMETHICONE; PHENOXYETHANOL; ERGOTHIONEINE; BISMUTH OXYCHLORIDE; OMEGA-3 FATTY ACIDS; COCONUT ALKANES; POLYHYDROXYSTEARIC ACID (2300 MW); ETHYLHEXYLGLYCERIN; HEXYLENE GLYCOL; CYPERUS ROTUNDUS ROOT; LONICERA JAPONICA FLOWER; XANTHIUM SIBIRICUM FRUIT; DIPROPYLENE GLYCOL; VITAMIN A PALMITATE; .ALPHA.-TOCOPHEROL ACETATE; OPUNTIA FICUS-INDICA STEM; SODIUM CITRATE; BETA CAROTENE; SALICYLIC ACID; ACETYL HEXAPEPTIDE-8; SORBIC ACID; LECITHIN, SOYBEAN; VINYL DIMETHICONE/METHICONE SILSESQUIOXANE CROSSPOLYMER; HEXYL LAURATE; ISOHEXADECANE; POLYGLYCERYL-4 ISOSTEARATE; HYDROGEN DIMETHICONE (13 CST); CYCLOMETHICONE 6; MAGNESIUM SULFATE, UNSPECIFIED; SACCHAROMYCES LYSATE; WATER; POTASSIUM SORBATE; VITIS VINIFERA ANTHOCYANINS; CYCLOMETHICONE 5; SILICON DIOXIDE; TRIETHOXYSILYLETHYL POLYDIMETHYLSILOXYETHYL HEXYL DIMETHICONE; CAPRYLYL GLYCOL; OLEA EUROPAEA LEAF; LAMINARIA DIGITATA; ISOMALT; FERRIC OXIDE YELLOW; POLYGLYCERYL-3 POLYDIMETHYLSILOXYETHYL DIMETHICONE (4000 MPA.S); MICA; ASCORBYL PALMITATE; SODIUM BENZOATE; DIMETHICONE; ALUMINUM OXIDE; SQUALANE; HYALURONIC ACID; TOCOPHEROL; FERRIC OXIDE RED

Drug Facts

Active Ingredients

Titanium Dioxide 6.5%

Zinc Oxide 8.5%

Purpose

Sunscreen

Uses

Helps prevent sunburn.

If used as directed with other sun protection measures (see Directions), decreases the risk of skin cancer and early skin aging caused by the sun.

Warnings

For external use only.

Do not use

On damaged or broken skin.

When using this product

Keep out of eyes. Rinse with water to remove

Stop use and ask a doctor if • Rash occurs.

Keep out of reach of children. • If swallowed, get medical help or contact a Poison Control Center right away.

DOSAGE AND ADMINISTRATION

Directions For Sunscreen Use • Apply generously 15 minutes before sun exposure. • Children under 6 months of age: ask a doctor. • Reapply at least every 2 hours. • Use a water resistant sunscreen if swimming or sweating: • immediately after towel drying. • at least every 2 hours.

OTHER SAFETY INFORMATION

Sun Protection Measures: Spending time in the sun increases your risk of skin cancer and early skin aging. To decrease this risk, regularly use a sunscreen with a Broad Spectrum SPF value of 15 or higher and other sun protection measures including: • limit time in the sun, especially from 10 a.m.-2 p.m. • wear long-sleeved shirts, pants, hats and sunglasses.

Other information • Protect the product in this container from excessive heat and direct sun.

INACTIVE INGREDIENT

Inactive Ingredients Water/Aqua/Eau, Coconut Alkanes, Cyclopentasiloxane, Squalane, Polyglyceryl-4 Diisostearate/Polyhydroxystearate/Sebacate, Glycerin, Silica, Cetyl PEG/PPG-10/1 Dimethicone, Hexyl Laurate, lsohexadecane, Polyglyceryl-4 Isostearate, Vinyl Dimethicone/Lauryl Dimethicone Crosspolymer, Hydrogen Dimethicone, Hydroxypropylcocoate PEG-8 Dimethicone, Dimethicone, Alumina, Polyglyceryl-3 Polydimethylsiloxyethyl Dimethicone, Cyclohexasiloxane, Magnesium Sulfate, Mica, Polyhydroxystearic Acid, Phenoxyethanol, Triethoxysilylethyl Polydimethylsiloxyethyl Hexyl Dimethicone, Caprylyl Glycol, Dimethicone/PEG-10/15 Crosspolymer, Ettylhexylglycerin, Hexylene Glycol, Dipotassium Glycyrrhizate, Perfluorodecalin, Zinc PCA, Saccharomyces Lysate Extract, Centella Asiatica Extract, Leuconostoc/Radish Root Ferment Filtrate, Olea Europaea (Olive) Leaf Extract, Artemisia Vulgads Extract, Hyaluronic Acid, Laminaria Digitata Extract, Phospholipids, lsomalt, Cyperus Rotundus Root Extract, Lonicera Japonica (Honeysuckle) Flower Extract, Xanthium Sibiricum Fruit Extract, Dipropylene Glycol, Retinyl PaImitate, Ascorbyl Palmitate, Tocopheryl Acetate, Opuntia Ficus-Indica Stem Extract, Sodium Citrate, Sodium Benzoate, Beta-Carotene, Potassium Sorbate, Salicylic Acid, Acetyl Hexapeptide-8, Sorbic Acid, Tocopherol, Lecithin, Vitis Vinifera (Grape) Fruit Cell Extract, Pentaerythrityl Tetra-Di-T-Butyl Hydroxyhydrocinnamate, Ergothioneine, Iron Oxides (CI 77492), Bismuth Oxychloride (CI 77163), Iron Oxides (CI 77491), Iron Oxides (CI 77499)